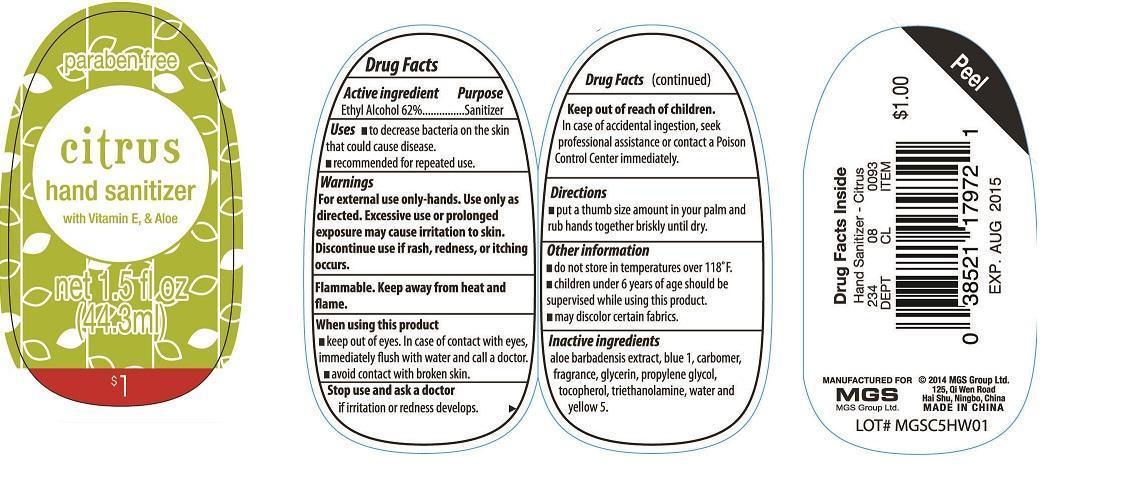 DRUG LABEL: Citrus Hand Sanitizer with vitamin E and aloe
NDC: 51263-3185 | Form: LIQUID
Manufacturer: MGS Group Limited
Category: otc | Type: HUMAN OTC DRUG LABEL
Date: 20140626

ACTIVE INGREDIENTS: ALCOHOL 62 mL/100 mL
INACTIVE INGREDIENTS: ALOE VERA LEAF; GLYCERIN; PROPYLENE GLYCOL; TOCOPHEROL; TROLAMINE; WATER

Drug Fact

Active Ingredient

Ethyl Alcohol 62%

Purpose

Sanitizer

Uses

- to decrease bacteria on the skin that could cause disease
- recommended for repeated use

Warnings

For external use only- hands.

Use only as directed

Excessive use or prolonged exposure may cause irritation to skin.

Discontinue use if rash, redness or itching occurs.

Flammable. Keep away from heat and flame.

When using this product

- keep out of eyes. In case of contact with eyes, immediately flush with water and call a doctor.
- avoid contact with broken skin.

Stop use and ask a doctor if

irritation or redness develops

Keep out of reach of children.

In case of accidental ingestion, seek professional assistance or contact a Poison Control Center immediately.

Directions

put a thumb size amount in your palm and rub hands together briskly until dry.

Other Information

- do not store in temperatures over 118F
- Children under 6 years of age should be supervised while using this product
- may discolor certain fabrics

Inactive Ingredients

aloe barbadensis gel, carbomer, fragrance, glycerin, propylene glycol, tocopherol, triethanolamine, water.

Product Labeling

Hand Sanitizer

net 1.5 fl oz (44.3mL)

Manufactured for

MGS Group, Ltd.

Made in China